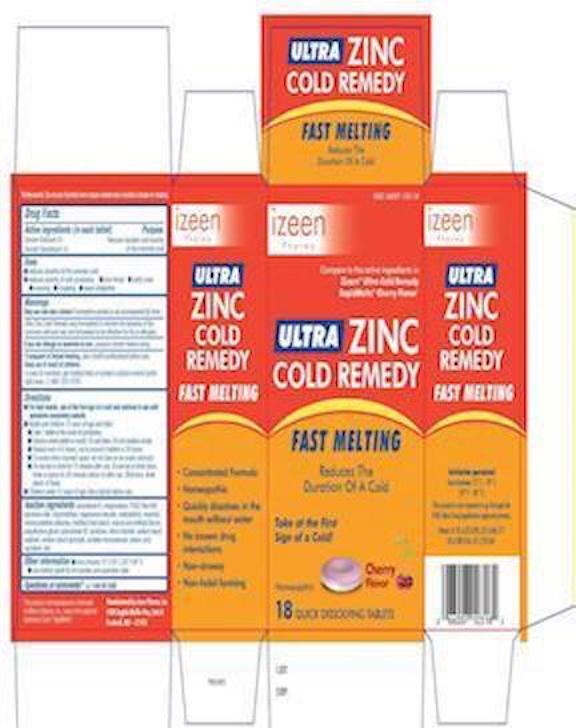 DRUG LABEL: Ultra Cold Remedy  Rapidmelts
NDC: 66007-103 | Form: TABLET
Manufacturer: Izeen Pharma, Inc.
Category: homeopathic | Type: HUMAN OTC DRUG LABEL
Date: 20150205

ACTIVE INGREDIENTS: ZINC ACETATE 2 [hp_X]/1 1; ZINC GLUCONATE 1 [hp_X]/1 1
INACTIVE INGREDIENTS: CROSPOVIDONE; FD&C RED NO. 40; ALUMINUM OXIDE; MAGNESIUM STEARATE; MANNITOL; AMMONIUM GLYCYRRHIZATE; SODIUM STARCH GLYCOLATE TYPE A POTATO; STEARIC ACID; SUCRALOSE

Ultra Zinc Cold Remedy Fast Melting -Cherry Flavor

Drug Facts

Active ingredients (in each tablet)

Zincum aceticum 2x
Zincum gluconicum 1x

Purpose

Reduces duration and severity of the common cold

Uses

- reduces duration of the common cold
- reduces the severity of cold symptoms:
  - sore throat
  - stuffy nose
  - sneezing
  - coughing
  - nasal congestion

Zicam® ULTRA Cold Remedy was formulated to shorten the duration of the common cold and was not formulated to be effective for flu or allergies.

Warnings

Ask a doctor before use if you have

- a sensitivity to zinc or are allergic to zinc

Stop use and ask a doctor if symptoms persist or are accompanied by fever

PREGNANCY OR BREAST FEEDING

If pregnant or breast-feeding, ask a health professional before use.

Keep out of reach of children. In case of overdose, get medical help or contact a Poison Control Center right away.

Directions

- for best results, use at the first sign of a cold and continue to use until symptoms completely subside
- adults and children 12 years of age and older:
  - take 1 tablet at the onset of symptoms
  - dissolve entire tablet in mouth. Do not chew. Do not swallow whole.
  - repeat every 4-6 hours, not to exceed 4 tablets in 24 hours
  - to avoid minor stomach upset, do not take on an empty stomach
  - do not eat or drink for 15 minutes after use. Do not eat or drink citrus fruits or juices for 30 minutes before or after use. Otherwise, drink plenty of fluids.
- children under 12 years of age: ask a doctor before use

Other information

- store between 15-29° (59-84°F)

Inactive ingredients

artificial flavor, crospovidone, FD&C red no. 40 aluminum lake, magnesium stearate, mannitol, monoammonium glycyrrhizinate, sodium starch glycolate, stearic acid, sucralose

Questions/Comments

Questions/Comments call 1-844-287-0260

Manufactured by Izeen Pharma, Inc. 6900 English Muffin Way, Unit A, Frederick, MD 21703

PRINCIPAL DISPLAY PANEL - 18 Tablet Carton

NDC# 66007-103-18